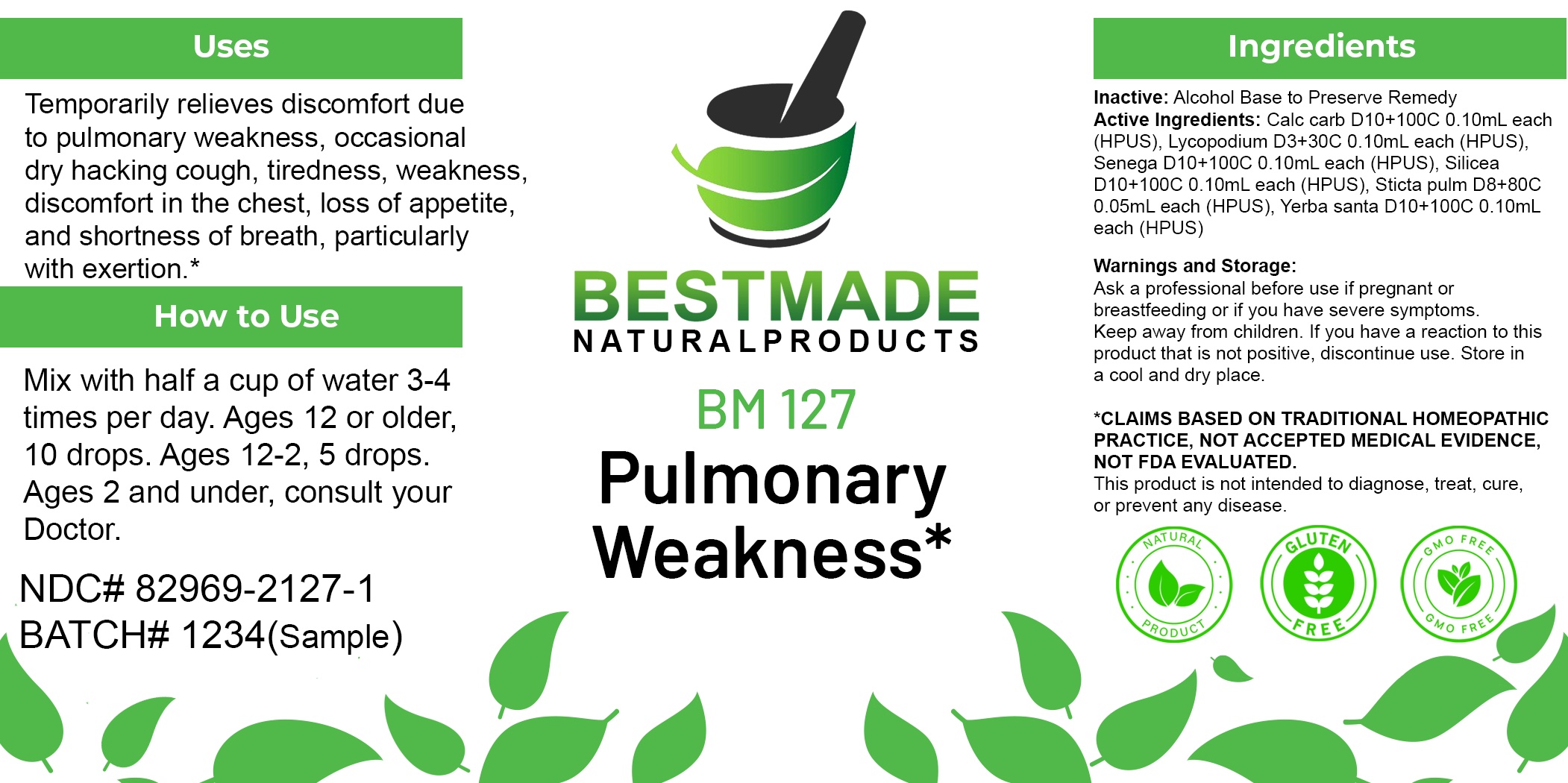 DRUG LABEL: Bestmade Natural Products BM127
NDC: 82969-2127 | Form: LIQUID
Manufacturer: Bestmade Natural Products
Category: homeopathic | Type: HUMAN OTC DRUG LABEL
Date: 20250210

ACTIVE INGREDIENTS: POLYGALA SENEGA ROOT 30 [hp_C]/30 [hp_C]; OYSTER SHELL CALCIUM CARBONATE, CRUDE 30 [hp_C]/30 [hp_C]; SILICON DIOXIDE 30 [hp_C]/30 [hp_C]; LYCOPODIUM CLAVATUM SPORE 30 [hp_C]/30 [hp_C]; LOBARIA PULMONARIA 30 [hp_C]/30 [hp_C]; ERIODICTYON CALIFORNICUM LEAF 30 [hp_C]/30 [hp_C]
INACTIVE INGREDIENTS: ALCOHOL 30 [hp_C]/30 [hp_C]

BM127

DOSAGE AND ADMINISTRATION

How to Use

Mix with half a cup of water 3-4 times per day. Ages 12 or older, 10 drops. Ages 12-2, 5 drops. Ages 2 and under, consult your Doctor.

Inactive:

Alcohol Base to Preserve Product

Active Ingredients:

Calc carb D10+100C 0.10mL each (HPUS), Lycopodium D3+30C 0.10mL each (HPUS), Senega D10+100C 0.10mL each (HPUS), Silicea D10+100C 0.10mL each (HPUS), Sticta pulm D8+80C 0.05mL each (HPUS), Yerba santa D10+100C 0.10mL each (HPUS)

Uses
Temporarily relieves discomfort due to pulmonary weakness, occasional dry hacking cough, tiredness, weakness, discomfort in the chest, loss of appetite, and shortness of breath, particularly with exertion.*

Uses
Temporarily relieves discomfort due to pulmonary weakness, occasional dry hacking cough, tiredness, weakness, discomfort in the chest, loss of appetite, and shortness of breath, particularly with exertion.*

KEEP OUT OF REACH OF CHILDREN

Warnings and Storage:

Ask a professional before use if pregnant or breastfeeding or if you have severe symptoms.

Keep away from children. If you have a reaction to this product that is not positive, discontinue use. Store in a cool and dry place

*CLAIMS BASED ON TRADITIONAL HOMEOPATHIC PRACTICE, NOT ACCEPTED MEDICAL EVIDENCE NOT FDA EVALUATED.
This product is not intended to diagnose, treat, cure, or prevent any disease.

Warnings and Storage:

Ask a professional before use if pregnant or breastfeeding or if you have severe symptoms.

Keep away from children. If you have a reaction to this product that is not positive, discontinue use. Store in a cool and dry place

*CLAIMS BASED ON TRADITIONAL HOMEOPATHIC PRACTICE, NOT ACCEPTED MEDICAL EVIDENCE NOT FDA EVALUATED.
This product is not intended to diagnose, treat, cure, or prevent any disease.

Entire package label